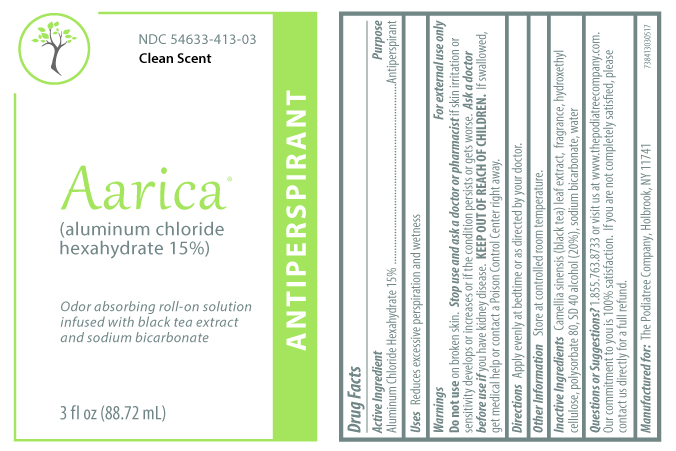 DRUG LABEL: Aarica
NDC: 54633-413 | Form: LIQUID
Manufacturer: The Podiatree Company
Category: otc | Type: HUMAN OTC DRUG LABEL
Date: 20171219

ACTIVE INGREDIENTS: ALUMINUM CHLORIDE 15 g/100 mL
INACTIVE INGREDIENTS: CAMELLIA SINENSIS WHOLE; HYDROXYETHYL CELLULOSE (100 MPA.S AT 2%); POLYSORBATE 80; ALCOHOL; SODIUM BICARBONATE; WATER

ACTIVE INGREDIENT

ALUMINUM CHLORIDE HEXAHYDRATE- 15%

PURPOSE

ANTIPERSPIRANT

USES

REDUCES EXCESSIVE PERSPIRATION AND WETNESS

WARNING

For external use only.

DO NOT USE ON BROKEN SKIN

STOP USE AND ASK A DOCTOR OR PHARMACIST IF SKIN IRRITATION OR SENSITIVITY DEVELOPS OR INCREASES OR IF THE CONDITION PERSISTS OR GETS WORSE

ASK A DOCTOR BEFORE USE IF YOU HAVE KIDNEY DISEASE.

Keep out of reach of children. If swallowed, get medical help or contact a Poison Control Center right away.

DIRECTIONS

APPLY EVENLY AT BEDTIME OR AS DIRECTED BY YOUR DOCTOR.

OTHER INFORMATION

STORE AT CONTROLLED ROOM TEMPERATURE.

INACTIVE INGREDIENT

INACTIVE INGREDIENTS: CAMELLIA SINENSIS (BLACK TEA) LEAF EXTRACT, FRAGRANCE, HYDROXYETHYL CELLULOSE, POLYSORBATE 80, SD 40 ALCOHOL (20%), SODIUM BICARBONATE, WATER

QUESTIONS

QUESTIONS OR SUGGESTIONS? 1.855.763.8733 or visit us at www.thepodiatreecompany.com